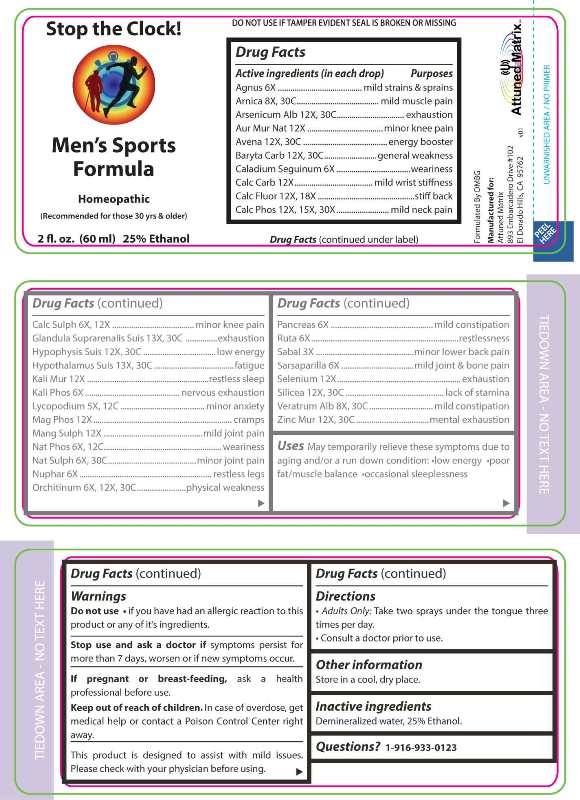 DRUG LABEL: Mens Sports Formula
NDC: 71144-0002 | Form: SPRAY
Manufacturer: Attuned Matrix, LLC
Category: homeopathic | Type: HUMAN OTC DRUG LABEL
Date: 20230502

ACTIVE INGREDIENTS: CHASTE TREE FRUIT 6 [hp_X]/1 mL; ARNICA MONTANA WHOLE 8 [hp_X]/1 mL; ARSENIC TRIOXIDE 12 [hp_X]/1 mL; SODIUM TETRACHLOROAURATE 12 [hp_X]/1 mL; AVENA SATIVA FLOWERING TOP 12 [hp_X]/1 mL; BARIUM CARBONATE 12 [hp_X]/1 mL; DIEFFENBACHIA SEGUINE WHOLE 6 [hp_X]/1 mL; OYSTER SHELL CALCIUM CARBONATE, CRUDE 12 [hp_X]/1 mL; CALCIUM FLUORIDE 12 [hp_X]/1 mL; TRIBASIC CALCIUM PHOSPHATE 12 [hp_X]/1 mL; CALCIUM SULFATE ANHYDROUS 6 [hp_X]/1 mL; SUS SCROFA ADRENAL GLAND 13 [hp_X]/1 mL; SUS SCROFA PITUITARY GLAND 12 [hp_X]/1 mL; SUS SCROFA HYPOTHALAMUS 13 [hp_X]/1 mL; POTASSIUM CHLORIDE 12 [hp_X]/1 mL; DIBASIC POTASSIUM PHOSPHATE 6 [hp_X]/1 mL; LYCOPODIUM CLAVATUM SPORE 5 [hp_X]/1 mL; MAGNESIUM PHOSPHATE, DIBASIC TRIHYDRATE 12 [hp_X]/1 mL; MANGANESE SULFATE 12 [hp_X]/1 mL; SODIUM PHOSPHATE, DIBASIC, HEPTAHYDRATE 6 [hp_X]/1 mL; SODIUM SULFATE 6 [hp_X]/1 mL; NUPHAR LUTEA ROOT 6 [hp_X]/1 mL; SUS SCROFA TESTICLE 6 [hp_X]/1 mL; SUS SCROFA PANCREAS 6 [hp_X]/1 mL; RUTA GRAVEOLENS FLOWERING TOP 6 [hp_X]/1 mL; SAW PALMETTO 3 [hp_X]/1 mL; SMILAX ORNATA ROOT 6 [hp_X]/1 mL; SELENIUM 12 [hp_X]/1 mL; SILICON DIOXIDE 12 [hp_X]/1 mL; VERATRUM ALBUM ROOT 8 [hp_X]/1 mL; ZINC CHLORIDE 12 [hp_X]/1 mL
INACTIVE INGREDIENTS: WATER; ALCOHOL

DRUG FACTS:

ACTIVE INGREDIENTS:

Agnus Castus 6X, Arnica Montana 8X, 30C, Arsenicum Album 12X, 30C, Aurum Muriaticum Natronatum 12X, Avena Sativa 12X, 30C, Baryta Carbonica 12X, 30C, Caladium Seguinum 6X, Calcarea Carbonica 12X, Calcarea Fluorica 12X, 18X, Calcarea Phosphorica 12X, 15X, 30X, Calcarea Sulphurica 6X, 12X, Glandula Suprarenalis Suis 13X, 30C, Hypophysis Suis 12X, 30C, Hypothalamus Suis 13X, 30C, Kali Muriaticum 12X, Kali Phosphoricum 6X, Lycopodium Clavatum 5X, 12C, Magnesia Phosphorica 12X, Manganum Sulphuricum 12X, Natrum Phosphoricum 6X, 12C, Natrum Sulphuricum 6X, 30C, Nuphar Luteum 6X, Orchitinum (Suis) 6X, 12X, 30C, Pancreas Suis 6X, Ruta Graveolens 6X, Sabal Serrulata 3X, Sarsaparilla (Smilax Regelii) 6X, Selenium Metallicum 12X, Silicea 12X, 30C, Veratrum Album 8X, 30C, Zincum Muriaticum 12X, 30C.

PURPOSE:

Agnus Castus – mild strains & sprains, Arnica Montana – mild muscle pain, Arsenicum Album - exhaustion, Aurum Muriaticum Natronatum – minor knee pain, Avena Sativa – energy booster, Baryta Carbonica – general weakness, Caladium Seguinum - weariness, Calcarea Carbonica – mild wrist stiffness, Calcarea Fluorica – stiff back, Calcarea Phosphorica – mild neck pain, Calcarea Sulphurica – minor knee pain, Glandula Suprarenalis Suis - exhaustion, Hypophysis Suis – low energy, Hypothalamus Suis - fatigue, Kali Muriaticum – restless sleep, Kali Phosphoricum – nervous exhaustion, Lycopodium Clavatum – minor anxiety, Magnesia Phosphorica - cramps, Manganum Sulphuricum – mild joint pain, Natrum Phosphoricum - weariness, Natrum Sulphuricum – minor joint pain, Nuphar Luteum – restless legs, Orchitinum – physical weakness, Pancreas – mild constipation, Ruta Graveolens - restlessness, Sabal Serrulata – minor lower back pain, Sarsaparilla – mild joint & bone pain, Selenium Metallicum - exhaustion, Silicea – lack of stamina, Veratrum Album – mild constipation, Zincum Muriaticum – mental exhaustion

USES:

May temporarily relieve these symptoms due to aging and/or a run down condition: •low energy •poor fat/muscle balance •occasional sleeplessness

WARNINGS:

Do not use •if you have had an allergic reaction to this product or any of its ingredients.

Stop use and ask a doctor if symptoms persist for more than 7 days, worsen or if new symptoms occur.

If pregnant or breast feeding, ask a health professional before use.

Keep out of reach of children. In case of overdose, get medical help or contact a Poison Control Center right away.

This product is designed to assist with mild issues.

Please check with your physicians before using.

DO NOT USE IF TAMPER EVIDENT SEAL IS BROKEN OR MISSING

Store in a cool, dry place.

KEEP OUT OF REACH OF CHILDREN:

In case of overdose, get medical help or contact a Poison Control Center right away.

DIRECTIONS:

• Adults Only: Take two sprays under the tongue three times per day.

• Consult a doctor prior to use.

INACTIVE INGREDIENTS:

Demineralized water, 25% Ethanol.

QUESTIONS:

Formulated By DMBG

Manufactured for:

Attuned Matrix

893 Embarcadero Drive #102

El Dorado Hills, CA 95762

(916) 850-5152

1-916-933-0123

PACKAGE LABEL DISPLAY:

Stop the Clock!

Men's Sports

Formula

Homeopathic

(Recommeneded for those 30 yrs & older)

2 fl. oz. (60ml)